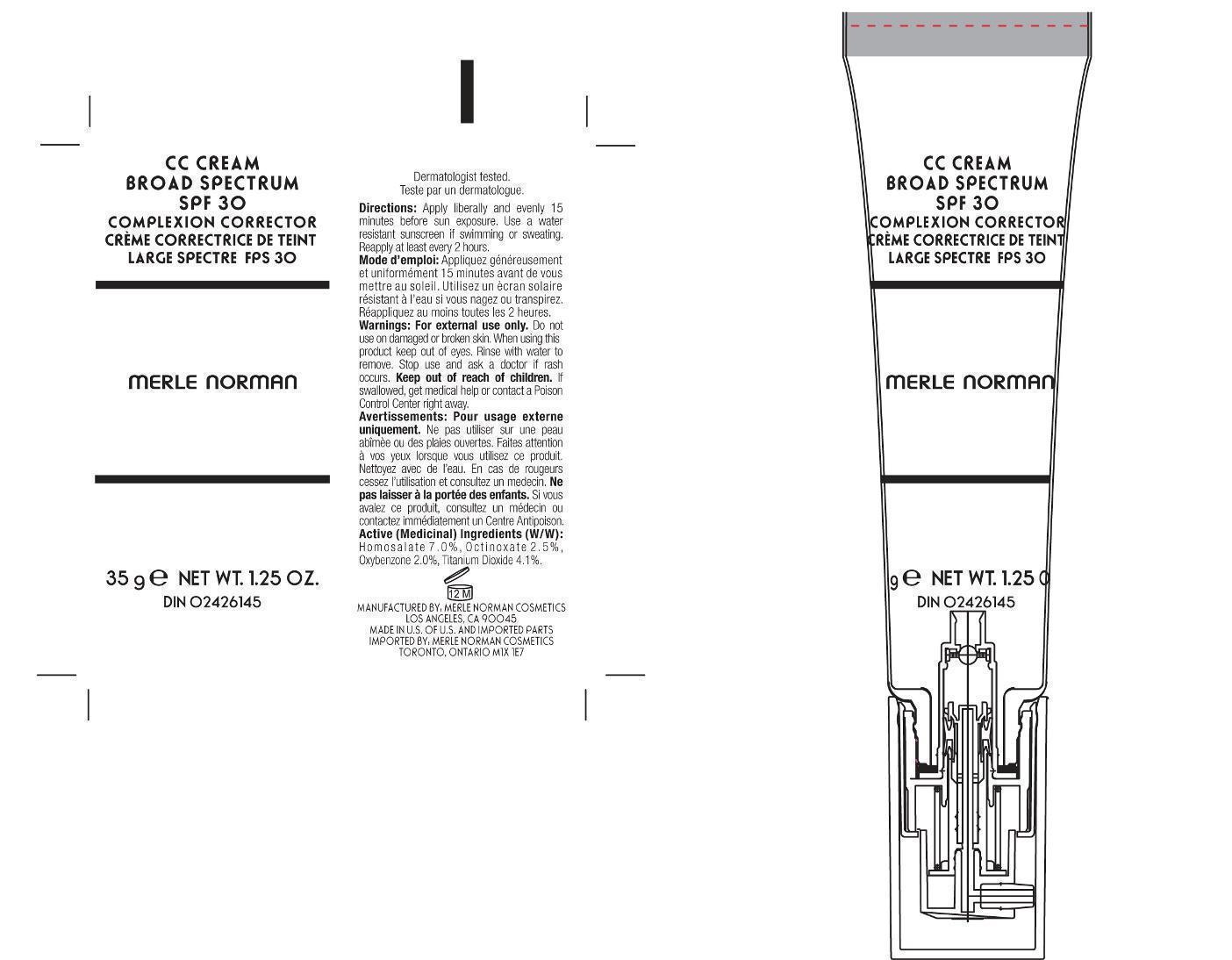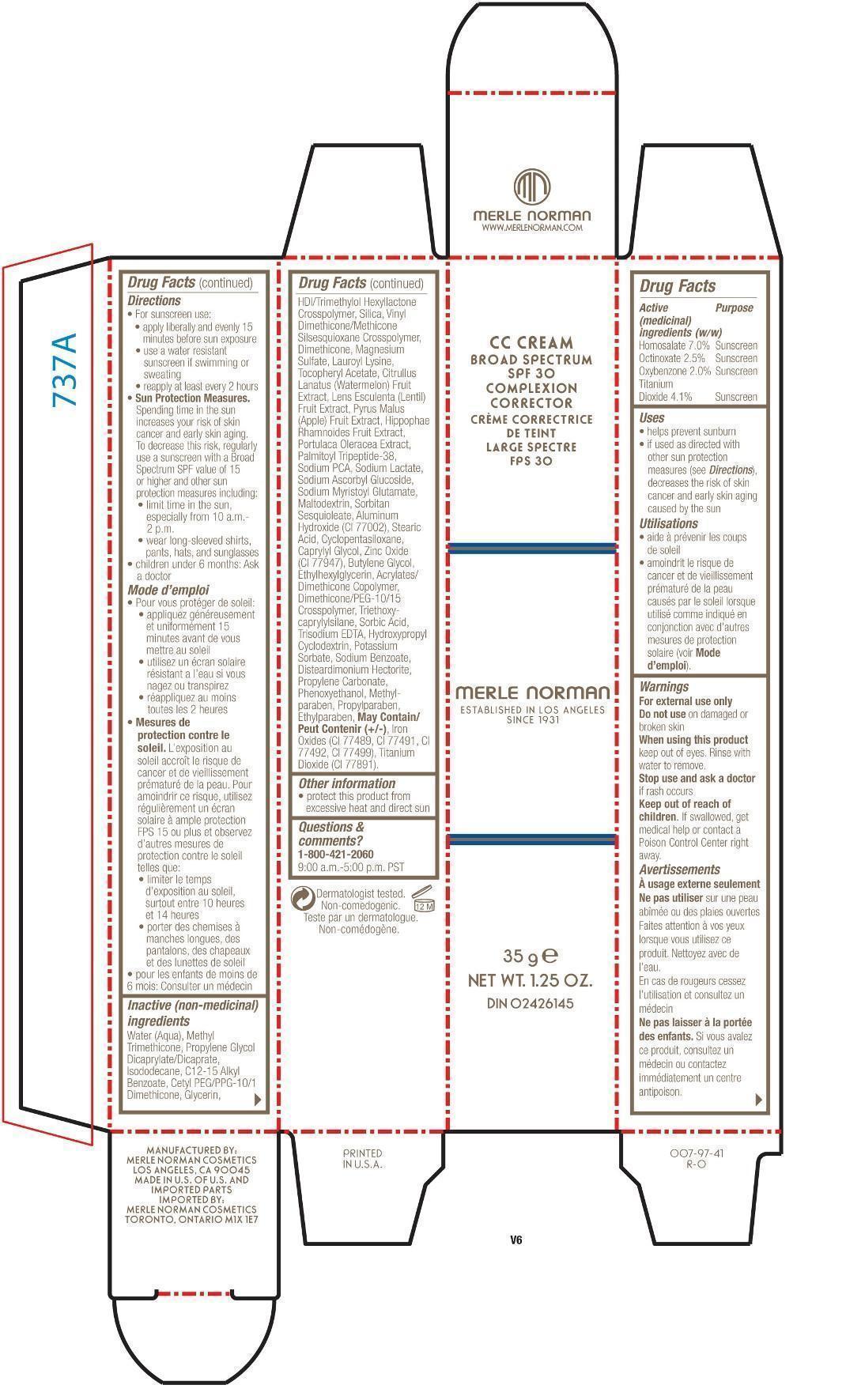 DRUG LABEL: CC Cream Broad Spectrum SPF 30
NDC: 57627-170 | Form: CREAM
Manufacturer: Merle Norman Cosmetics, Inc
Category: otc | Type: HUMAN OTC DRUG LABEL
Date: 20251120

ACTIVE INGREDIENTS: HOMOSALATE 7 g/100 g; OCTINOXATE 2.5 g/100 g; OXYBENZONE 2 g/100 g; TITANIUM DIOXIDE 4.1 g/100 g
INACTIVE INGREDIENTS: SODIUM MYRISTOYL GLUTAMATE; MALTODEXTRIN; SORBITAN SESQUIOLEATE; SODIUM LACTATE; ALUMINUM HYDRIDE; STEARIC ACID; CYCLOMETHICONE 5; CAPRYLYL GLYCOL; ZINC OXIDE; BUTYLENE GLYCOL; ETHYLHEXYLGLYCERIN; TRIETHOXYCAPRYLYLSILANE; SORBIC ACID; EDETATE TRISODIUM; POTASSIUM SORBATE; SODIUM BENZOATE; DISTEARDIMONIUM HECTORITE; PROPYLENE CARBONATE; PHENOXYETHANOL; METHYLPARABEN; ETHYLPARABEN; FERROUS OXIDE; FERRIC OXIDE RED; FERROSOFERRIC OXIDE; WATER; METHYL TRIMETHICONE; PROPYLENE GLYCOL DICAPRYLATE/DICAPRATE; ISODODECANE; ALKYL (C12-15) BENZOATE; CETYL PEG/PPG-10/1 DIMETHICONE (HLB 2); GLYCERIN; SILICON DIOXIDE; DIMETHICONE; MAGNESIUM SULFATE, UNSPECIFIED FORM; LAUROYL LYSINE; .ALPHA.-TOCOPHEROL ACETATE; WATERMELON; LENS CULINARIS FRUIT; APPLE; HIPPOPHAE RHAMNOIDES FRUIT; PURSLANE; SODIUM PYRROLIDONE CARBOXYLATE

CC Cream Broad Spectrum SPF 30

Active (medicinal) Ingredients (w/w) Purpose
Homosalate 7.0% Sunscreen

Octinoxate 2.5% Sunscreen

Oxybenzone 2.0% Sunscreen

Titanium Dioxide 4.1% Sunscreen

Uses

• helps prevent sunburn

• if used as directed withother sun protection measures (see Directions), decreases the risk of skin cancer and early skin aging caused by the sun

Utilisations

• aide à prévenir les coups de soleil

• amoindrit le risque de cancer et de vieillissement prématuré de la peau causés par le soleil lorsque utilisé comme indiqué en conjonction avec d’autres mesures de protection solaire (voir Mode d’emploi).

Keep out of reach of children

Stop use and ask a doctor if rash occurs. En cas de rougeurs cessez l'utilisationet consultez un medecin.

Warnings

For external use only

Do not use on damaged or broken skin When using this product

keep out of eyes. Rinse with water to remove.

If swallowed, get medical help or contact a Poison Control Center right away.

Avertissements

À usage externe seulement

Ne pas utilisersur une peau abîmée ou des plaies ouvertes

Faites attention à vos yeux

lorsque vous utilisez ce produit. Nettoyez avec de l’eau.

Ne pas laisser à la portée des enfants.

Si vous avalez ce produit, consultez un médecin ou contactez immédiatement un centre antipoison.

Drug Facts

Directions

• For sunscreen use:

• apply liberally and evenly 15 minutes before sun exposure

• use a water resistant sunscreen if swimming or sweating

• reapply at least every 2 hours

•Sun Protection Measures.

Spending time in the sun increases your risk of skin cancer and early skin aging.

To decrease this risk, regularly use a sunscreen with a Broad Spectrum SPF value of 15 or higher and other sun protection measures including:

• limit time in the sun, especially from 10 a.m.-2 p.m.

• wear long-sleeved shirts, pants, hats, and sunglasses

• children under 6 months: Ask a doctor

Mode d’emploi

• Pour vous protéger de soleil:

• appliquez généreusement et uniformément 15 minutes avant de vous mettre au soleil

• utilisez un écran solaire résistant a l’eau si vous nagez ou transpirez

• réappliquez au moins toutes les 2 heures

• Mesures de protection contre le soleil.

L’exposition au soleil accroît le risque de cancer et de vieillissement prématuré de la peau. Pour amoindrir ce risque, utilisez

régulièrement un écran solaire à ample protection FPS 15 ou plus et observez d’autres mesures de protection contre le soleil

telles que:

• limiter le temps d’exposition au soleil, surtout entre 10 heures et 14 heures

• porter des chemises à manches longues, des pantalons, des chapeaux et des lunettes de soleil

• pour les enfants de moins de 6 mois: Consulter un médecin

Inactive (non-medicinal)ingredients

Water (Aqua), Methy l Trimethicone, Propylene Glycol Dicaprylate/Dicaprate, Isododecane, C12-15 Alkyl Benzoate, Cetyl PEG/PPG-10/1 Dimethicone, Glycerin, HDI/Trimethylol Hexyllactone Crosspolymer, Silica, Vinyl Dimethicone/Methicone Silsesquioxane Crosspolymer, Dimethicone, Magnesium Sulfate, Lauroyl Lysine, Tocopheryl Acetate, CitrullusLanatus (Watermelon) Fruit Extract, Lens Esculenta (Lentil) Fruit Extract, Pyrus Malus(Apple) Fruit Extract, Hippophae Rhamnoides Fruit Extract,Portulaca Oleracea Extract,Palmitoyl Tripeptide-38, Sodium PCA, Sodium Lactate,Sodium Ascorbyl Glucoside, Sodium Myristoyl Glutamate,Maltodextrin, Sorbitan Sesquioleate, Aluminum Hydroxide (CI 77002), Stearic Acid, Cyclopentasiloxane, Caprylyl Glycol, Zinc Oxide (CI 77947), Butylene Glycol, Ethylhexylglycerin, Acrylates/ Dimethicone Copolymer, Dimethicone/PEG-10/15 Crosspolymer, Triethoxycaprylylsilane, Sorbic Acid, Trisodium EDTA, Hydroxypropyl Cyclodextrin, Potassium Sorbate, Sodium Benzoate, Disteardimonium Hectorite, Propylene Carbonate, Phenoxyethanol, Methylparaben, Propylparaben, Ethylparaben,

May Contain/ Peut Contenir (+/-), Iron Oxides (CI 77489, CI 77491, CI 77492, CI 77499), Titanium Dioxide (CI 77891).

PACKAGE LABEL

CC Cream Broad Spectrum SPF 30

Complexion Corrector

Creme Correctrice de Teint

Large Spectre FPS 30

Merle Norman

35 g Net Wt. 1.25 oz